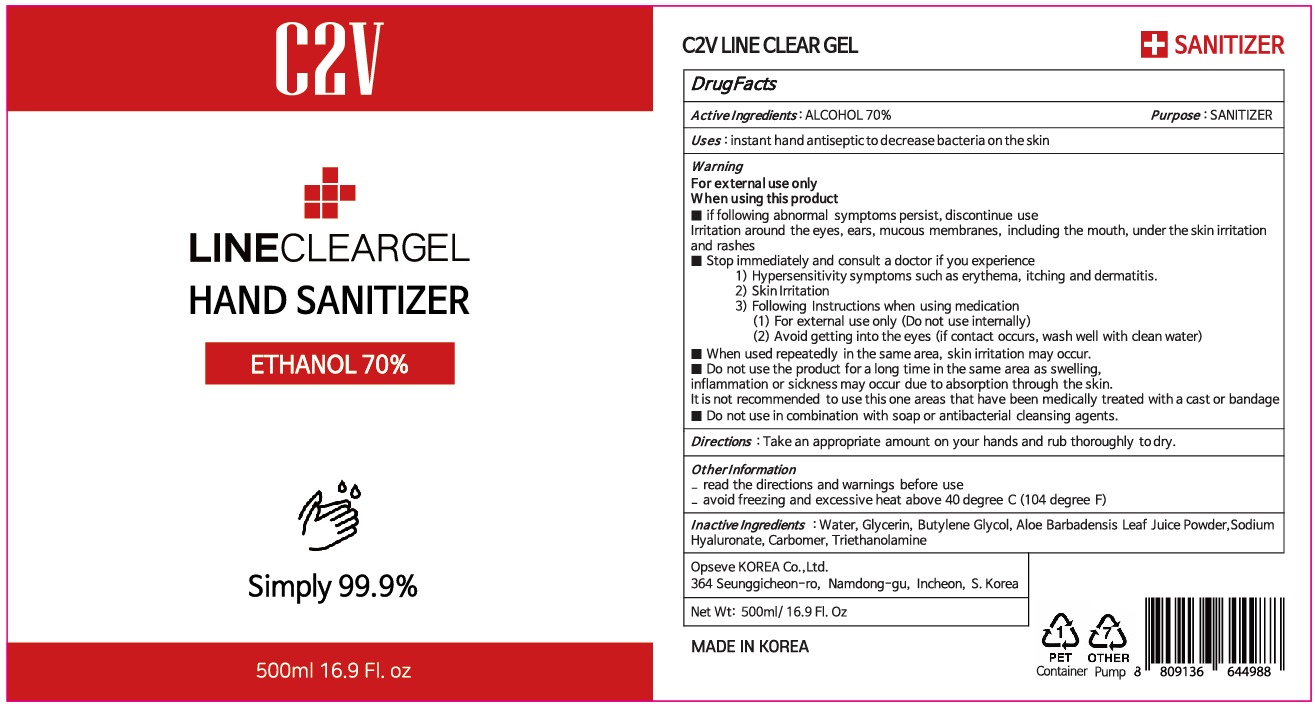 DRUG LABEL: C2V LINE CLEAR
NDC: 74195-030 | Form: GEL
Manufacturer: Opseve KOREA Co.,Ltd.
Category: otc | Type: HUMAN OTC DRUG LABEL
Date: 20200407

ACTIVE INGREDIENTS: ALCOHOL 350 g/500 mL
INACTIVE INGREDIENTS: Water; Glycerin; Butylene Glycol; ALOE VERA LEAF; HYALURONATE SODIUM; CARBOMER HOMOPOLYMER, UNSPECIFIED TYPE; TROLAMINE

ACTIVE INGREDIENT

Active ingredients: ALCOHOL 70%

INACTIVE INGREDIENT

Inactive ingredients:

Water, Glycerin, Butylene Glycol, Aloe Barbadensis Leaf Juice Powder, Sodium Hyaluronate, Carbomer, Triethanolamine

PURPOSE

Purpose: SANITIZER

WARNINGS

For external use only
When using this product
■ if following abnormal symptoms persist, discontinue use
Irritation around the eyes, ears, mucous membranes, including the mouth, under the skin irritation and rashes
■ Stop immediately and consult a doctor if you experience
1) Hypersensitivity symptoms such as erythema, itching and dermatitis.
2) Skin Irritation
3) Following Instructions when using medication
(1) For external use only (Do not use internally)
(2) Avoid getting into the eyes (if contact occurs, wash well with clean water)
■When used repeatedly in the same area, skin irritation may occur.
■Do not use the product for a long time in the same area as swelling, inflammation or sickness may occur due to absorption through the skin.
It is not recommended to use this one areas that have been medically treated with a cast or bandage.
■Do not use in combination with soap or antibacterial cleansing agents.

KEEP OUT OF REACH OF CHILDREN

Uses

instant hand antiseptic to decrease bacteria on the skin

Directions

Take an appropriate amount on your hands and rub thoroughly to dry.

Other Information

- read the directions and warnings before use
- avoid freezing and excessive heat above 40 degree C (104 degree F)